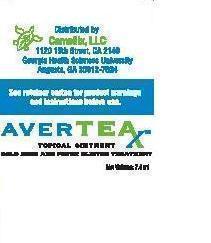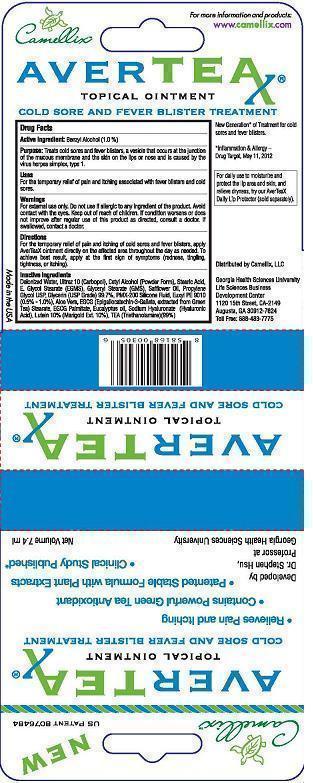 DRUG LABEL: AVERTEAX
NDC: 54866-002 | Form: CREAM
Manufacturer: Camellix, LLC
Category: otc | Type: HUMAN OTC DRUG LABEL
Date: 20140307

ACTIVE INGREDIENTS: BENZYL ALCOHOL 10 mg/1 g
INACTIVE INGREDIENTS: WATER; CARBOMER COPOLYMER TYPE A; CETYL ALCOHOL; STEARIC ACID; GLYCOL STEARATE; GLYCERYL MONOSTEARATE; Safflower Oil; Propylene Glycol; Glycerin; DIMETHICONE; PHENOXYETHANOL; ALOE VERA LEAF; EPIGALLOCATECHIN GALLATE STEARATES; EPIGALLOCATECHIN GALLATE PALMITATES; EUCALYPTUS OIL; Hyaluronic Acid; LUTEIN; CALENDULA OFFICINALIS FLOWER; TROLAMINE

AVERTEX Benzyl Alcohol

Active ingredient Purpose
Benzyl Alcohol (1.0%) Cold Sores & Fever blisters

PURPOSE:

Treats cold sores and fever blisters, a vesicle that occurs at the junction of the mucous membrane and the skin on the lips or nose and is caused by the virus herpes simplex, type 1.

ASK DOCTOR:

If condition worsens or does not improve after regular use of the product as directed, consult a doctor.

If swallowed, contact a doctor.

WARNINGS:

For external use only.

DIRECTIONS:

For the temporary relief of pain and itching of cold sores and fever blisters, apply AverTeaX ointment directly on the affected area throughout the day as needed. To achieve best result, apply at the frist sign of symptons (redness, tingling, tightness, or itching.)

STOP USE:

If illergic to any ingridient of the product.

INDICATIONS & USAGE:

Indications are for pain and itching associated with fever blisters and cold sores.

For the temporary Relief of Pain and itching associated with fever blisters and cold sores.

DO NOT USE:

If allergic to any ingredient of the product.

KEEP OUT OF REACH OF CHILDREN:

- If swallowed, contact a doctor.

INACTIVE INGREDIENT

Ultrez 10 (Carbopol), Cetyl Alcohol (Powder Form), Stearic Acid, E. Glycol Stearate (EGMS), Glyceryl Stearate (GMS), Safflower Oil, Propylene Glycol USP, Glycerin (USP Grade) 99.7%, PMX-200 Silicone Fluid, Euxyl PE 9010 (0.5% - 1.0%), Aloe Vera, EGCG (Epigallocatechin-3-Gallate, Extracted from Green Tea) Stearate, EGCG Palmitate, Eucalyptus oil, Sodium Hyaluronate (Hyaluronic Acid), Lutein 10% (Marigold Ext. 10%), TEA (Triethanolamine)(99%).

PACKAGE LABEL

AVERTEAX TOPICAL OINTMENT COLD SORES AND FEVER BLISTERS TREATMENT DISTRIBUTED BY CAMELLIX MADE IN USA